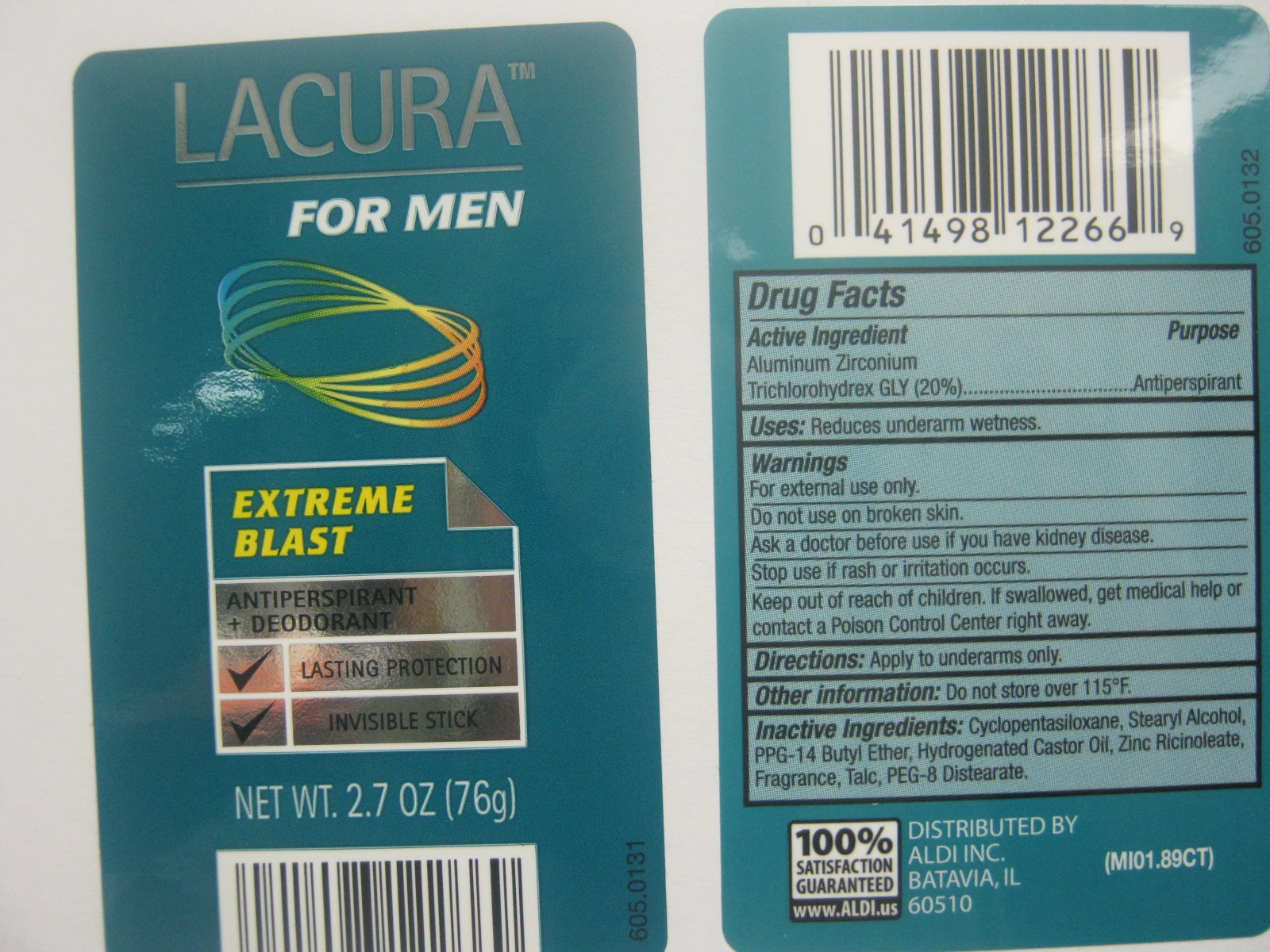 DRUG LABEL: Lacura Extreme Blast
NDC: 10889-110 | Form: STICK
Manufacturer: VVF Kansas Services LLC
Category: otc | Type: HUMAN OTC DRUG LABEL
Date: 20101117

ACTIVE INGREDIENTS: ALUMINUM ZIRCONIUM TRICHLOROHYDREX GLY 250 mg/1 g
INACTIVE INGREDIENTS: Stearyl Alcohol; PPG-14 Butyl  Ether; Hydrogenated Castor Oil; Zinc Ricinoleate; Talc; PEG-8 Distearate

Lacura Extreme Blast (Aluminun Zirconium Trichlorohydrex Gly)

ACTIVE INGREDIENT

Aluminum Zirconium Trichlorohydrex Gly 20%

PURPOSE

Anti-perspirant

USES

Reduces underarm wetness.

WARNINGS

For external use only.

Do not use on broken skin.

Ask a doctor before you use if you have kidney disease.

Stop use if rash or irritation occurs.

Keep out of reach of children.

If swallowed get medical help or contact a Poison Control Center immediately.

Directions

Apply evenly to underarms only.

STORAGE AND HANDLING

Do not store over 115 degrees F

Inactive Ingredients

Cyclopentasiloxane, Stearyl Alcohol, PPG-14 Butyl Ether, Hydrogenated Castor Oil, Zinc Ricinoleate, Fragrance, Talc, PEG-8 Distearate.

Distributed By:

ALDI INC.
BATAVIA, IL
60510
(MI01.89CT)
100% Satisfaction Guaranteed
www.ALDI.us

KEEP OUT OF REACH OF CHILDREN

If swallowed, get medical help or contact a Poison Control Center immediately.

PACKAGE LABEL

Lacura
For Men
Extreme Blast
Antiperspirant +Deodorant
Lasting Protection
Invisible Stick
NET WT. 2.7OZ (76g)